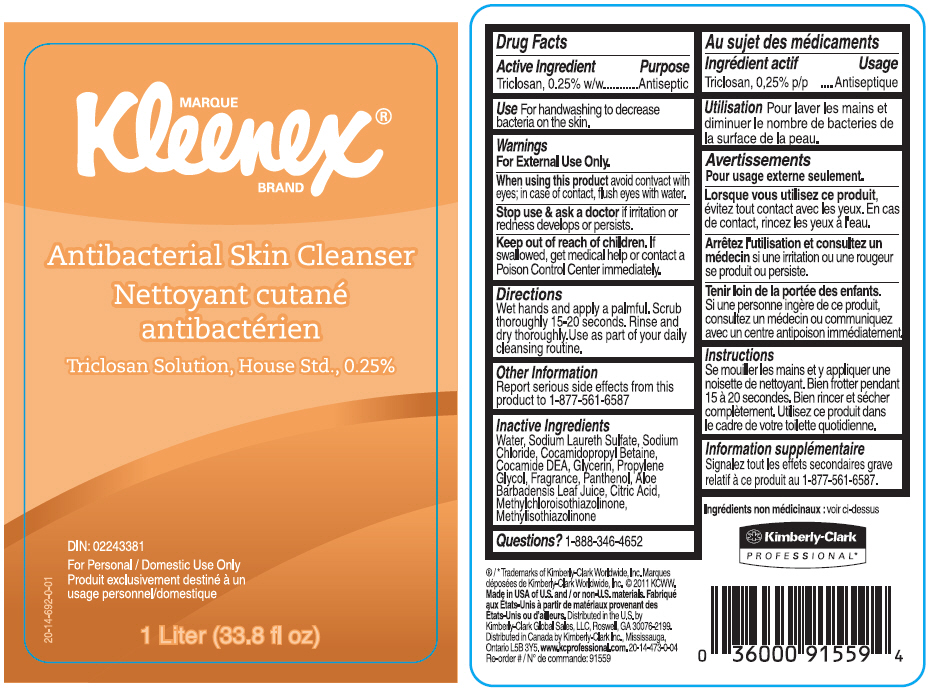 DRUG LABEL: KLEENEX Antibacterial Skin Cleanser 								
NDC: 55118-575 | Form: SOLUTION
Manufacturer: Kimberly-Clark Corporation
Category: otc | Type: HUMAN OTC DRUG LABEL
Date: 20140926

ACTIVE INGREDIENTS: Triclosan 2.5 g/1 L
INACTIVE INGREDIENTS: Water; Sodium Laureth-3 Sulfate; Sodium Chloride; Cocamidopropyl Betaine; Coco Diethanolamide; Glycerin; Methylchloroisothiazolinone; Methylisothiazolinone; Propylene Glycol; Panthenol; Aloe Vera Leaf; Citric Acid Monohydrate

KLEENEX® Antibacterial Skin Cleanser

Drug Facts

Active Ingredient

Triclosan, 0.25% w/w

Purpose

Antiseptic

Use

For handwashing to decrease bacteria on the skin.

Warnings

For External Use Only.

When using this product avoid contvact with eyes; in case of contact, flush eyes with water.

Stop use & ask a doctor if irritation or redness develops or persists.

Keep out of reach of children. If swallowed, get medical help or contact a Poison Control Center immediately.

Directions

Wet hands and apply a palmful. Scrub thoroughly 15-20 seconds. Rinse and dry thoroughly. Use as part of your daily cleansing routine.

Other Information

Report serious side effects from this product to 1-877-561-6587

Inactive Ingredients

Water, Sodium Laureth Sulfate, Sodium Chloride, Cocamidopropyl Betaine, Cocamide DEA, Glycerin, Propylene Glycol, Fragrance, Panthenol, Aloe Barbadensis Leaf Juice, Citric Acid, Methylchloroisothiazolinone, Methylisothiazolinone

Questions?

1-888-346-4652

Distributed in the U.S. by
Kimberly-Clark Global Sales, LLC, Roswell, GA 30076-2199.
Distributed in Canada by Kimberly-Clark Inc., Mississauga, Ontario L5B 3Y5.

PRINCIPAL DISPLAY PANEL - 1 Liter Container Label

MARQUE
Kleenex®
BRAND

Antibacterial Skin Cleanser

Triclosan Solution, House Std., 0.25%

DIN: 02243381

For Personal / Domestic Use Only

1 Liter (33.8 fl oz)

20-14-692-0-01